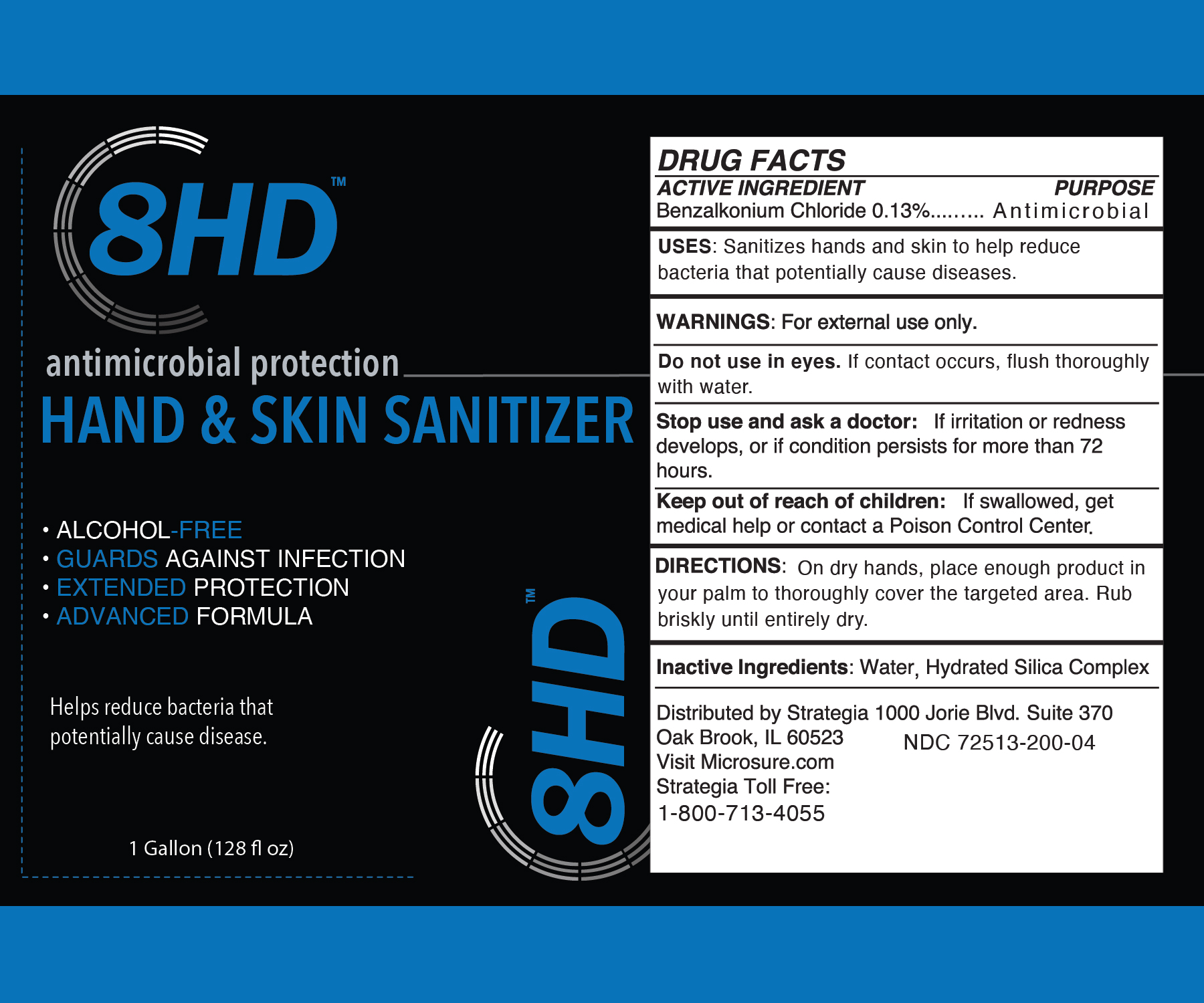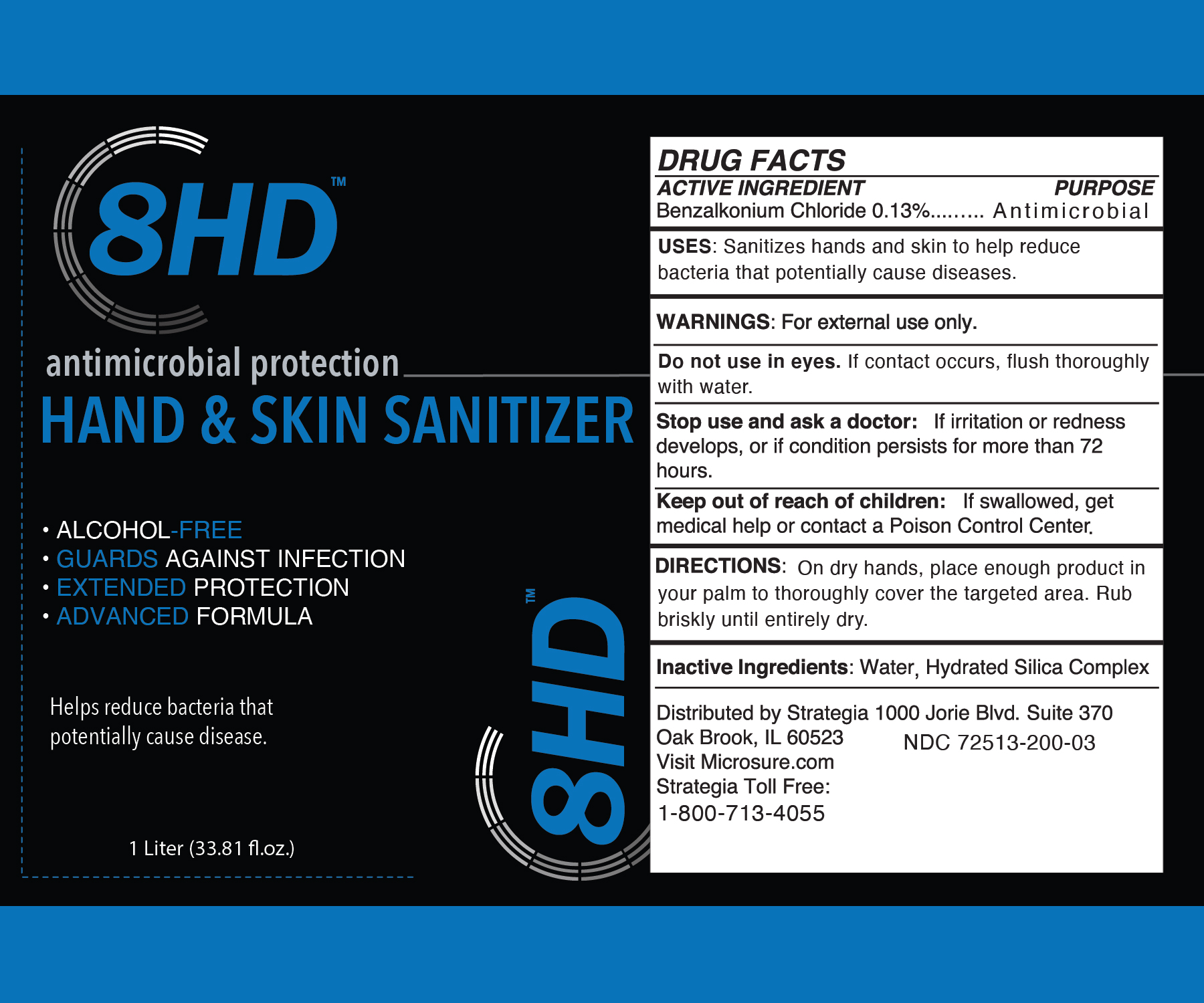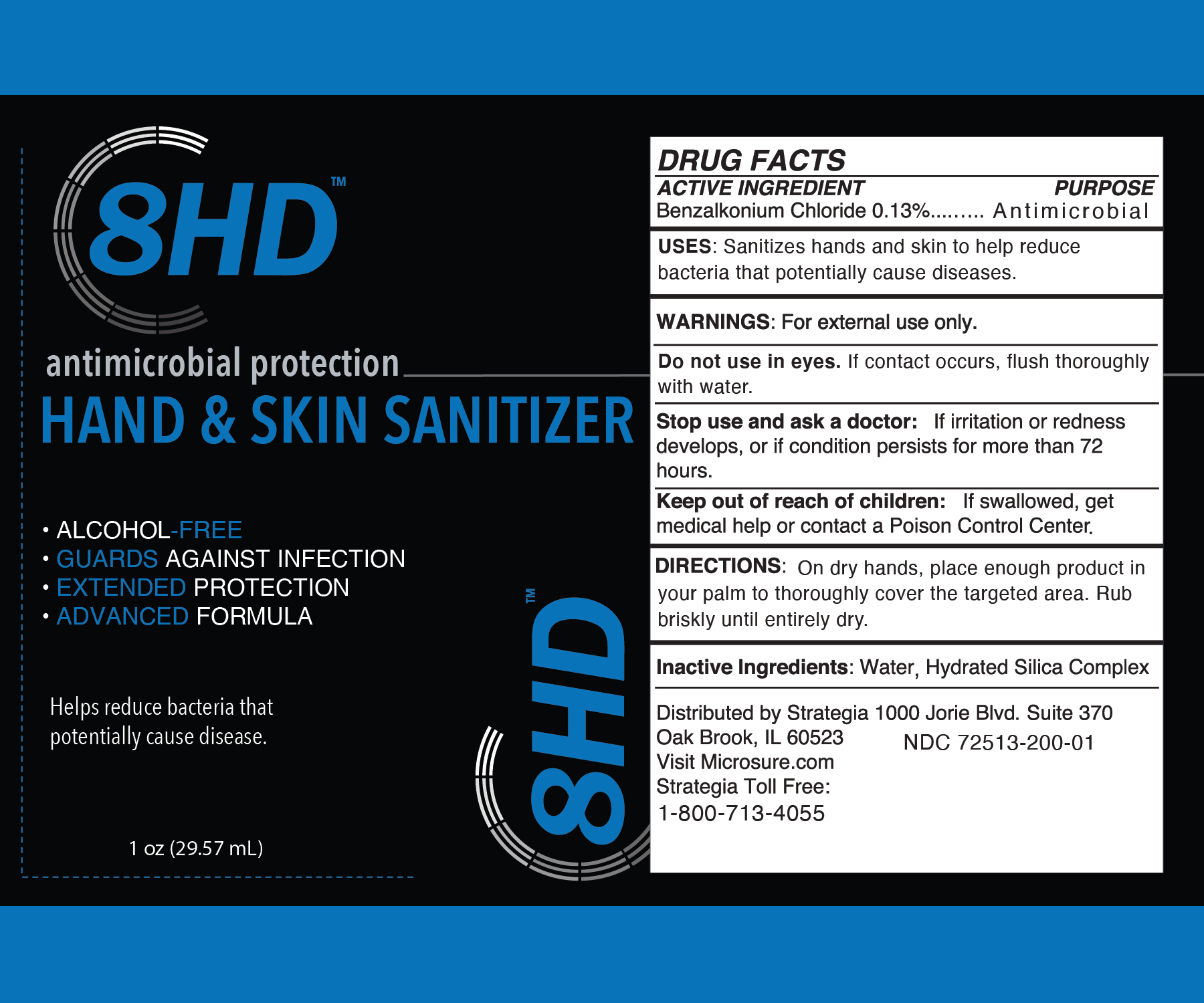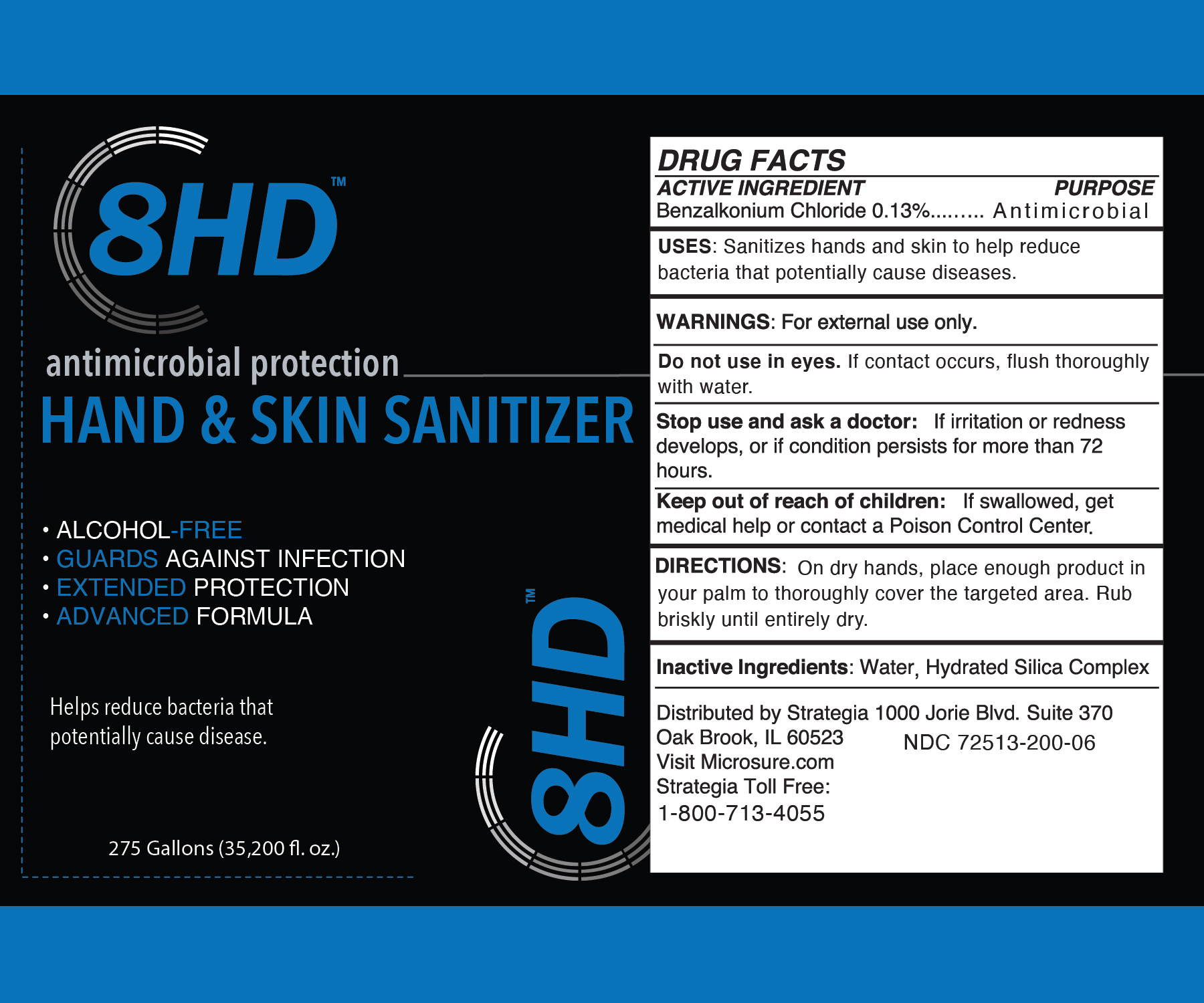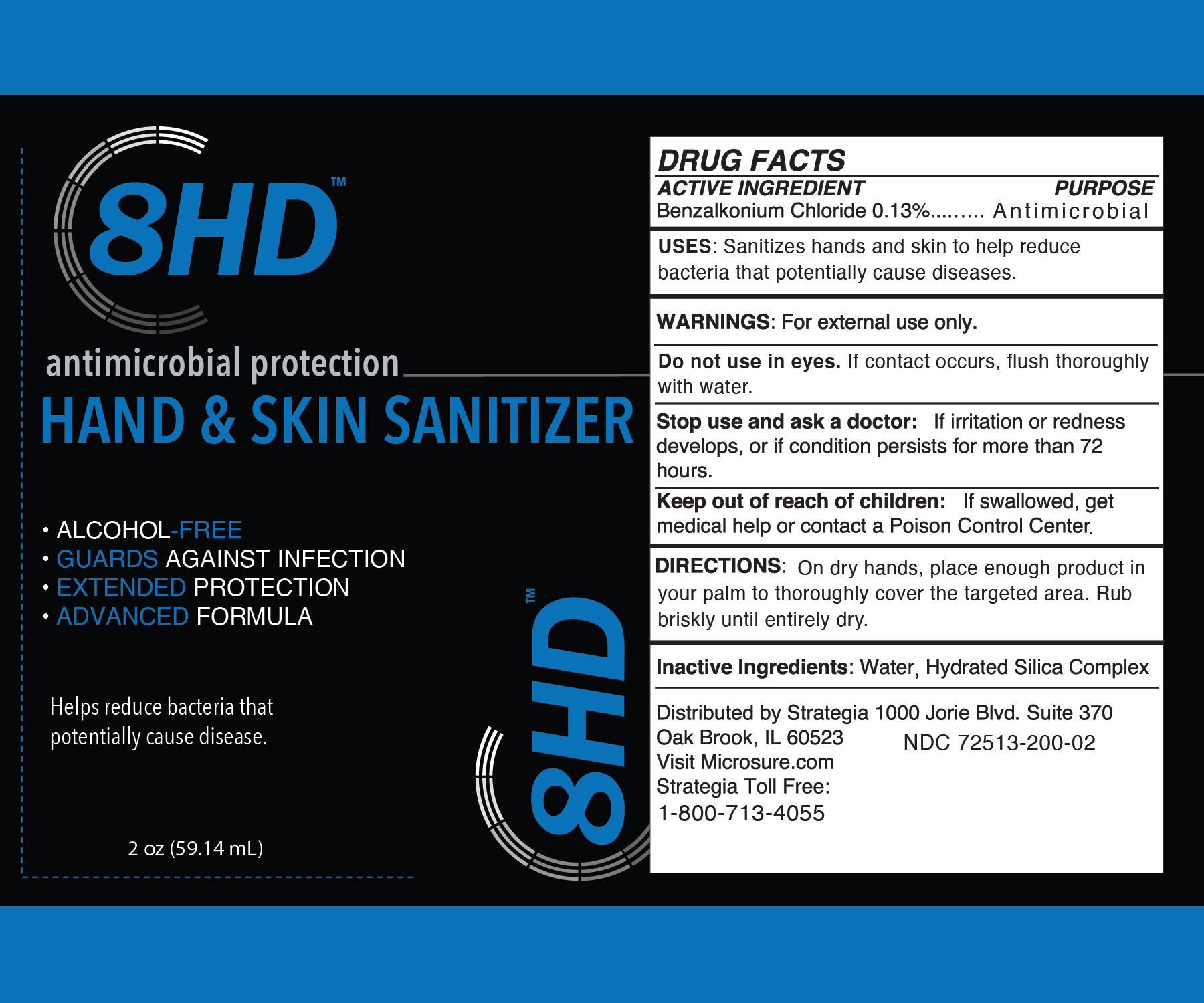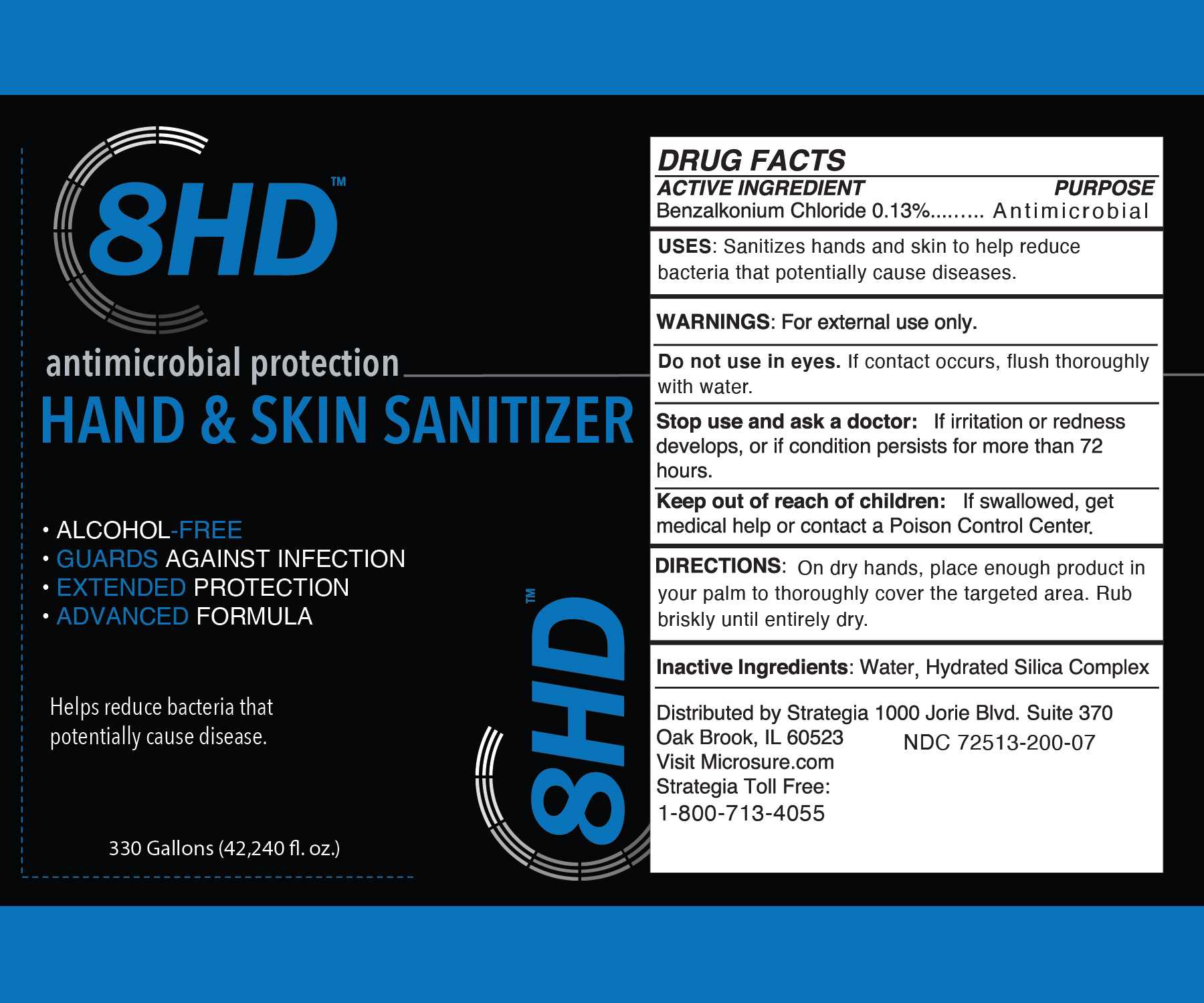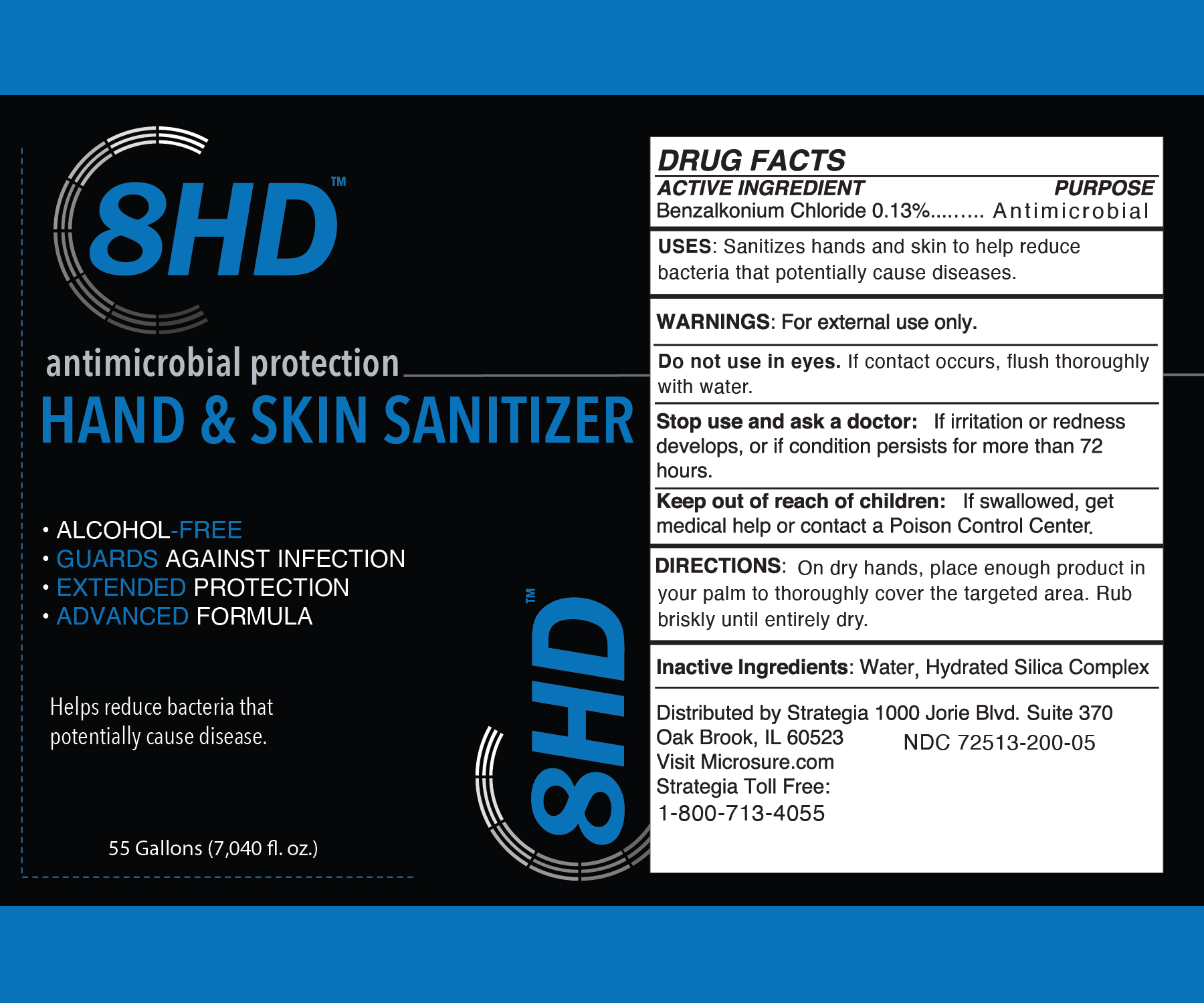 DRUG LABEL: 8HD Hand and Skin Sanitizer
NDC: 72513-200 | Form: LIQUID
Manufacturer: Strategia Project Management, Inc.
Category: otc | Type: HUMAN OTC DRUG LABEL
Date: 20231220

ACTIVE INGREDIENTS: BENZALKONIUM CHLORIDE 0.13 g/100 mL
INACTIVE INGREDIENTS: HYDRATED SILICA 0.04 g/100 mL; WATER 99.83 g/100 mL

8HD Hand and Skin Sanitizer

ACTIVE INGREDIENT

Benzalkonium Chloride 0.13%

PURPOSE

Antimicrobial

USES:

Sanitizes hands and skin to help reduce bacteria that potentially cause diseases.

WARNINGS:

For external use only.

Do not use

in eyes. If contact occurs, flush thoroughly with water.

Stop use and ask a doctor:

If irritation or redness develops, or if condition persists for more than 72 hours.

Keep out of reach of children:

If swallowed, get medical help or contact a Poison Control Center.

DIRECTIONS:

On dry hands, place enough product in your palms to thoroughly cover the targeted area. Rub briskly until entirely dry.

Inactive Ingredients:

Water, Hydrated Silica Complex